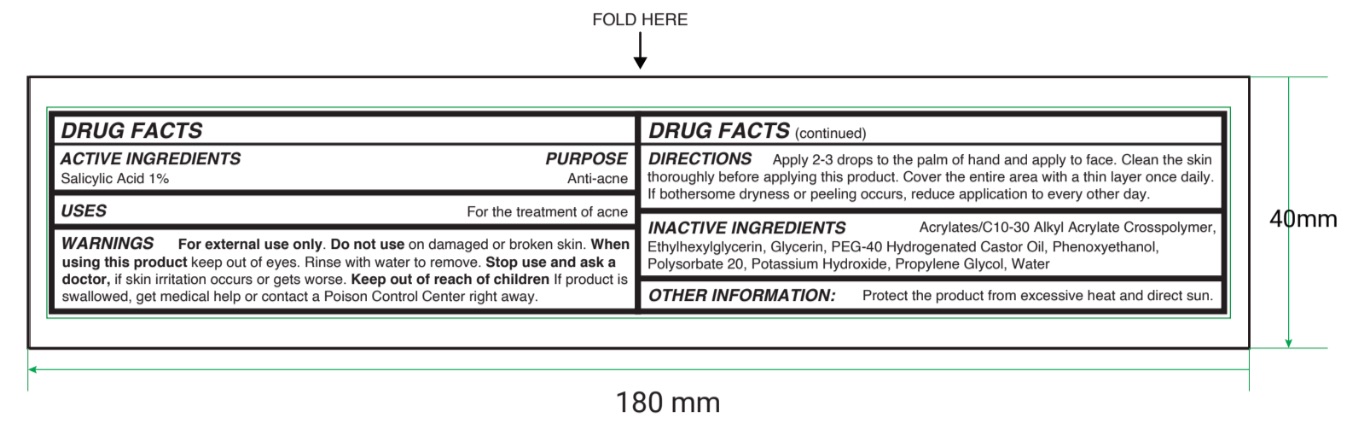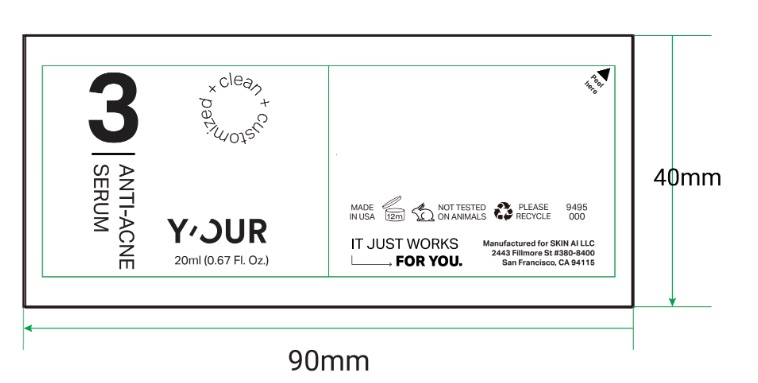 DRUG LABEL: YOUR Anti Acne Serum
NDC: 84229-0016 | Form: LIQUID
Manufacturer: Skin Ai, LLC
Category: otc | Type: HUMAN OTC DRUG LABEL
Date: 20251210

ACTIVE INGREDIENTS: SALICYLIC ACID 0.2 g/20 mL
INACTIVE INGREDIENTS: PHENOXYETHANOL; POLYOXYL 40 HYDROGENATED CASTOR OIL; POTASSIUM HYDROXIDE; PROPYLENE GLYCOL; ACRYLATES/C10-30 ALKYL ACRYLATE CROSSPOLYMER (60000 MPA.S); POLYSORBATE 20; WATER; GLYCERIN; ETHYLHEXYLGLYCERIN

YOUR Anti Acne Serum 20 ml (0.67 fl oz) 2024

Active ingredient

Salicylic Acid 1%

Purpose

Anti-acne

Uses

For the treatment of acne

Warnings

- For external use only

Do not use

on damaged or broken skin.

When using this product

keep out of eyes. Rinse with water to remove.

Stop use and ask a doctor

if skin irritation occurs or gets worse.

Keep out of reach of children.

If product is swallowed, get medical help or contact a Poison Control Center right away.

Directions

Apply 2-3 drops to the palm of hand and apply to face. Clean the skin thoroughly before applying this product. Cover the entire area with a thin layer once daily. If bothersome dryness or peeling occurs, reduce application to every other day.

Inactive ingredients

Water (Aqua), Propylene Glycol, Polysorbate 20, PEG-40 Hydrogenated Castor Oil, Glycerin, Phenoxyethanol, Potassium Hydroxide, Acrylates/C10-30 Alkyl Acrylate Crosspolymer, Ethylhexylglycerin.

Other information

Protect the product from excessive heat and direct sun.

Principal Display Panel

clean + customized

3

ANTI-ACNE

SERUM

Y'OUR

20 ml (0.67 Fl. Oz.)